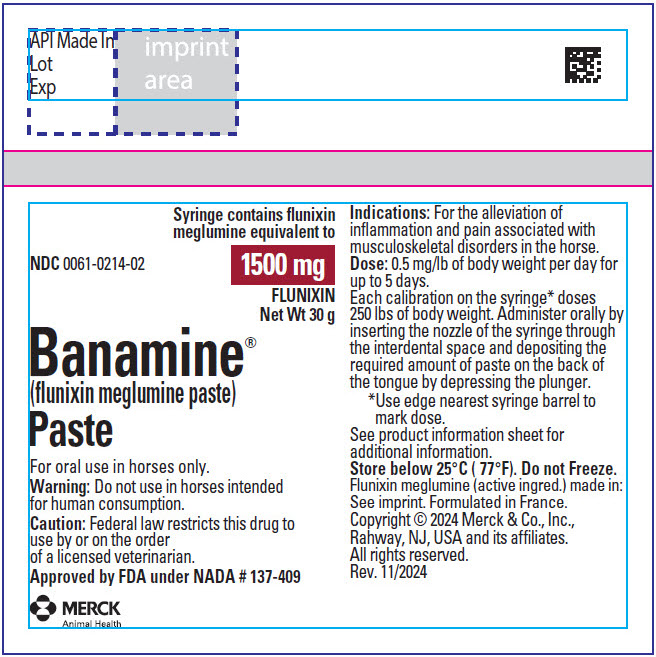 DRUG LABEL: Banamine
NDC: 0061-0214 | Form: PASTE
Manufacturer: Merck Sharp & Dohme Corp.
Category: animal | Type: PRESCRIPTION ANIMAL DRUG LABEL
Date: 20250430

ACTIVE INGREDIENTS: FLUNIXIN MEGLUMINE 1500 mg/30 g

Banamine®
(flunixin meglumine paste)

Paste –1500 mg
flunixin/syringe
Veterinary

For Oral Use in Horses Only

PRODUCT
INFORMATION

WARNINGS

CAUTION Federal law restricts this drug to use by or on the order of a licensed veterinarian.

DESCRIPTION

DESCRIPTION Each 30-g syringe of BANAMINE Paste contains flunixin meglumine equivalent to 1500 mg flunixin.

VETERINARY INDICATIONS

INDICATIONS BANAMINE Paste is recommended for the alleviation of inflammation and pain associated with musculoskeletal disorders in the horse.

ACTIVITY Flunixin meglumine is a potent, nonnarcotic, nonsteroidal, analgesic agent with anti-inflammatory and antipyretic activity. It is significantly more potent than pentazocine, meperidine, and codeine as an analgesic in the rat yeast paw test. Oral studies in the horse show onset of flunixin activity occurs within 2 hours of administration. Peak response occurs between 12 and 16 hours and duration of activity is 24 to 36 hours.

CONTRAINDICATIONS

CONTRAINDICATIONS There are no known contraindications to this drug when used as directed.

FOOD SAFETY WARNING

WARNING Do not use in horses intended for human consumption.

PRECAUTIONS

PRECAUTIONS The effect of BANAMINE Paste on pregnancy has not been determined. Studies to date show there is no detrimental effect on stallion spermatogenesis with or following the recommended dose of BANAMINE Paste.

SIDE EFFECTS During field studies with BANAMINE Paste, no significant side effects were reported.

DOSAGE AND ADMINISTRATION The recommended dose of flunixin is 0.5 mg per lb of body weight once daily. The BANAMINE Paste syringe, calibrated in twelve 250-lb weight increments, delivers 125 mg of flunixin for each 250 lbs (see dosage table). One syringe will treat a 1000-lb horse once daily for 3 days, or three 1000-lb horses one time.

DOSAGE TABLE
Syringe Mark [Use dial edge nearest syringe barrel to mark dose.] | Horse Weight (lbs) | BANAMINE Paste Delivered (g) | Mg Flunixin Delivered
0 | — | — | —
250 | 250 | 2.5 | 125
500 | 500 | 5.0 | 250
750 | 750 | 7.5 | 375
1000 | 1000 | 10.0 | 500

The paste is orally administered by inserting the nozzle of the syringe through the interdental space, and depositing the required amount of paste on the back of the tongue by depressing the plunger.

Treatment may be given initially by intravenous or intramuscular injection of BANAMINE Solution, followed by BANAMINE Granules or BANAMINE Paste on Days 2 to 5. BANAMINE treatment should not exceed 5 consecutive days.

TOXICITY No toxic effects were observed in rats given oral flunixin 2 mg/kg per day for 42 days. Higher doses produced ulceration of the gastrointestinal tract. The emetic dose in dogs is between 150 and 250 mg/kg. Flunixin was well tolerated in monkeys dosed daily with 4 mg/kg for 56 days. No adverse effects occurred in horses dosed orally with 1.0 or 1.5 mg/lb for fifteen consecutive days.

HOW SUPPLIED

HOW SUPPLIED BANAMINE Paste, 1500 mg is available in a single 30-g syringe.

STORAGE AND HANDLING

Store below 25°C (77°F). Do not Freeze.

For patent information: http://www.merck.com/product/patent/home.html

PRINCIPAL DISPLAY PANEL - 1500 mg Syringe Label

Syringe contains flunixin
meglumine equivalent to
1500 mg
FLUNIXIN
Net Wt 30 g

NDC 0061-0214-02

Banamine®
(flunixin meglumine paste)
Paste

For oral use in horses only.
Warning: Do not use in horses intended
for human consumption.
Caution: Federal law restricts this drug to
use by or on the order
of a licensed veterinarian.
Approved by FDA under NADA # 137-409

MERCK
Animal Health